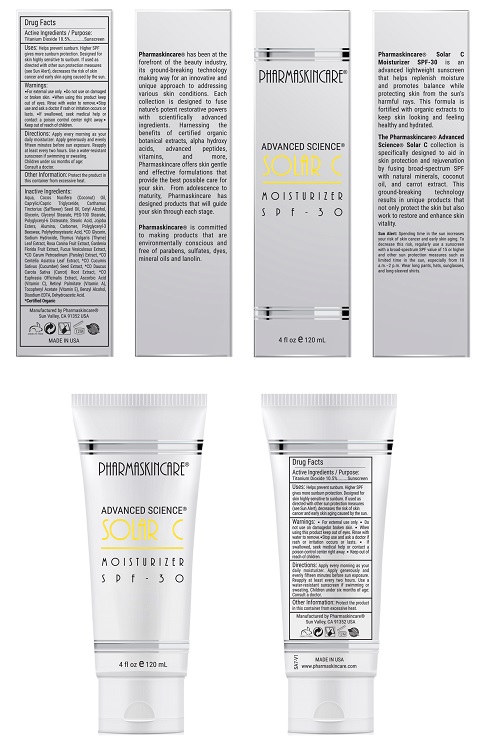 DRUG LABEL: Pharmaskincare Solar-C Moisturizer SPF 30
NDC: 68062-9099 | Form: LOTION
Manufacturer: Spa de Soleil
Category: otc | Type: HUMAN OTC DRUG LABEL
Date: 20181227

ACTIVE INGREDIENTS: TITANIUM DIOXIDE 0.2625 mg/2.5 mL
INACTIVE INGREDIENTS: MEDIUM-CHAIN TRIGLYCERIDES; WATER; COCONUT OIL; SAFFLOWER OIL; CETYL ALCOHOL; GLYCERIN

Pharmaskincare Solar-C Moisturizer SPF 30

Active Ingredient

Titanium Dioxide 10.5%

Purpose

Sunscreen

Warnings

- For external use only.
- Do not use on broken or damaged skin
- When using this product, keep out of eyes. Rinse with water to remove.
- Stop use and ask a doctor is rash or irritation occurs or lasts.
- If swallowed, seek medical help or contact a poison control center right away.
- Keep out of reach of children.

Directions

Apply every morning as a daily moisturizer. Apply generously and evenly 15 minutes before sun exposure. Reapply at least every two hours. Use a water-resistant sunscreen if swimming or sweating. Children under six months of age: consult a doctor before use.

Other Information

Protect the product in this container from excessive heat.

Uses:

Helps prevent sunburn. Higher SPF gives more sunburn protection. Designed for skin highly sensitive to sunburn. If used as directed with other sun protection measures (see Sun Alert) decreases the risk of skin cancer and early skin aging caused by the sun.

Sun Alert: Spending time in the use increases your risk of skin cancer and early skin aging. To decrease this risk, regularly use a sunscreen with a broad-spectrum SPF value of 15 or higher and other sun protection measures such as limited time in the sun, especially from 10 a.m. to 2 p.m. Wear long pants, hats, sunglasses, and long-sleeve shirts.

Inactive Ingredients:

Water, Cocos Nucifera (Coconut) Oil, Carthamus Tinctorius (Safflower) Seed Oil, Cetyl Alcohol, Caprylic/Capric Triglyceride, Glycerin, Glyceryl Stearate, PEG-100 Stearate, Titanium Dioxide, Polyglyceryl-3 Beeswax, Polyglyceryl-6 Distearate, Jojoba Esters, Polyhydroxystearic Acid, Carbomer, *CO Glycerin, Sodium Hydroxide, Thymus Vulgaris (Thyme) Leaf Extract, Rosa Canina Fruit Extract, Gardenia Florida Fruit Extract, Fucus Vesiculosus Extract, *CO Carum Petroselinum (Parsley) Extract, *CO Centella Asiatica Leaf Extract, *CO Cucumis Sativus (Cucumber) Seed Extract, *CO Daucus Carota Sativa (Carrot) Root Extract, *CO Euphrasia Officinalis Extract, Benzyl Alcohol, Disodium EDTA, Dehydroacetic Acid

Warning

Keep out of reach of children.

PACKAGE LABEL

Pharmaskincare SolarC SPF 30